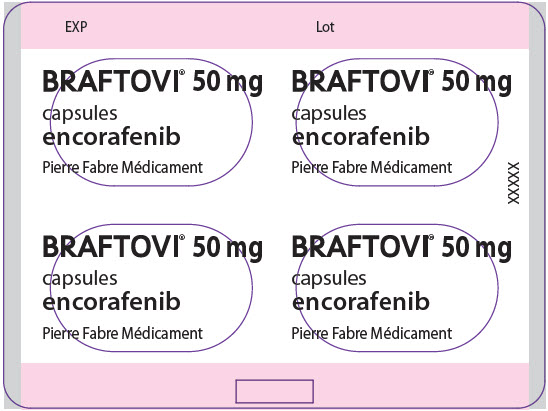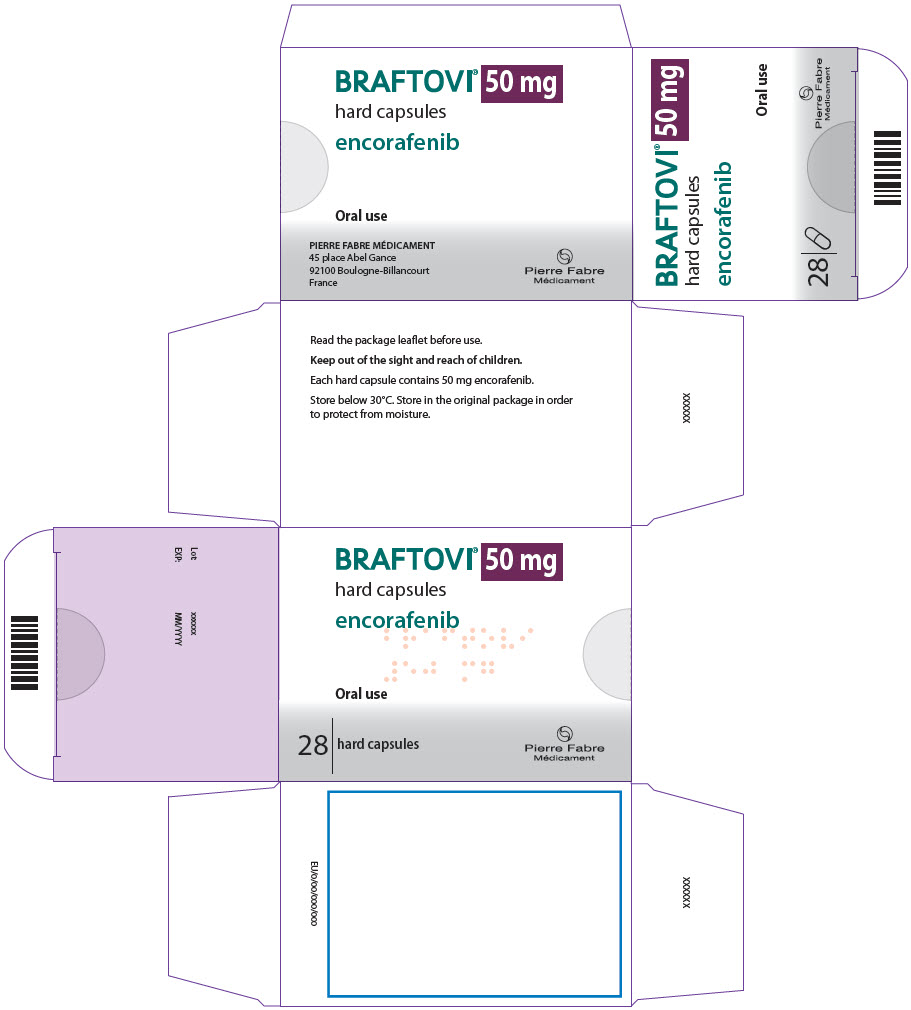 DRUG LABEL: BRAFTOVI
NDC: 70255-050 | Form: CAPSULE
Manufacturer: Array BioPharma Inc.
Category: prescription | Type: HUMAN PRESCRIPTION DRUG LABEL
Date: 20250729

ACTIVE INGREDIENTS: ENCORAFENIB 50 mg/1 1
INACTIVE INGREDIENTS: COPOVIDONE K25-31; POLOXAMER 188; MICROCRYSTALLINE CELLULOSE; SUCCINIC ACID; CROSPOVIDONE, UNSPECIFIED; SILICON DIOXIDE; MAGNESIUM STEARATE; GELATIN, UNSPECIFIED; TITANIUM DIOXIDE; FERRIC OXIDE RED; FERRIC OXIDE YELLOW; FERROSOFERRIC OXIDE; SHELLAC; PROPYLENE GLYCOL

BRAFTOVI® 50 mg

PRINCIPAL DISPLAY PANEL - 50 mg Capsule Blister Pack

EXP
Lot

BRAFTOVI® 50 mg

capsules
encorafenib

Pierre Fabre Médicament

XXXXX

PRINCIPAL DISPLAY PANEL - 50 mg Capsule Blister Pack Carton

BRAFTOVI® 50 mg

hard capsules

encorafenib

Oral use

28 | hard capsules

Pierre Fabre
Médicament